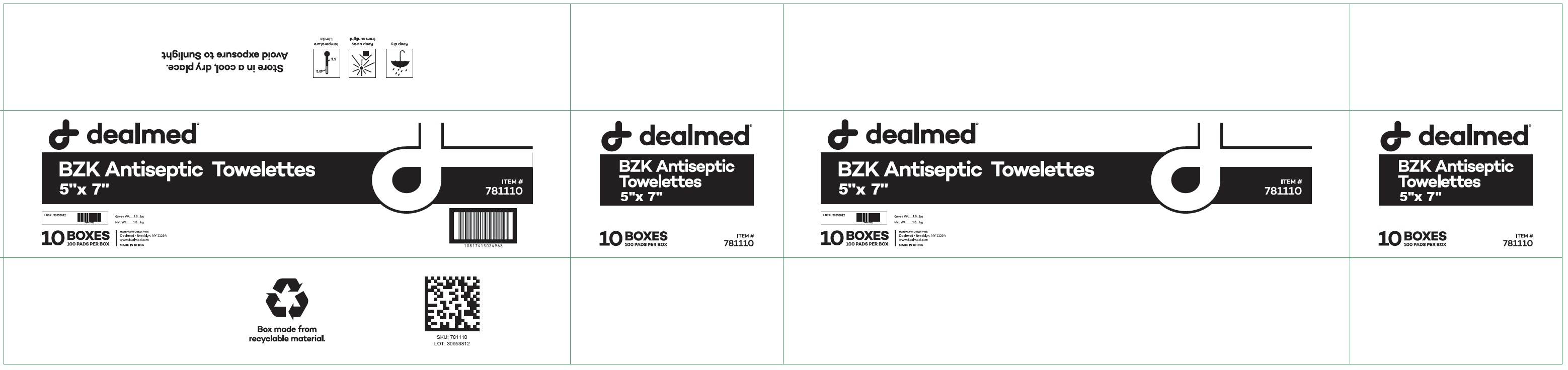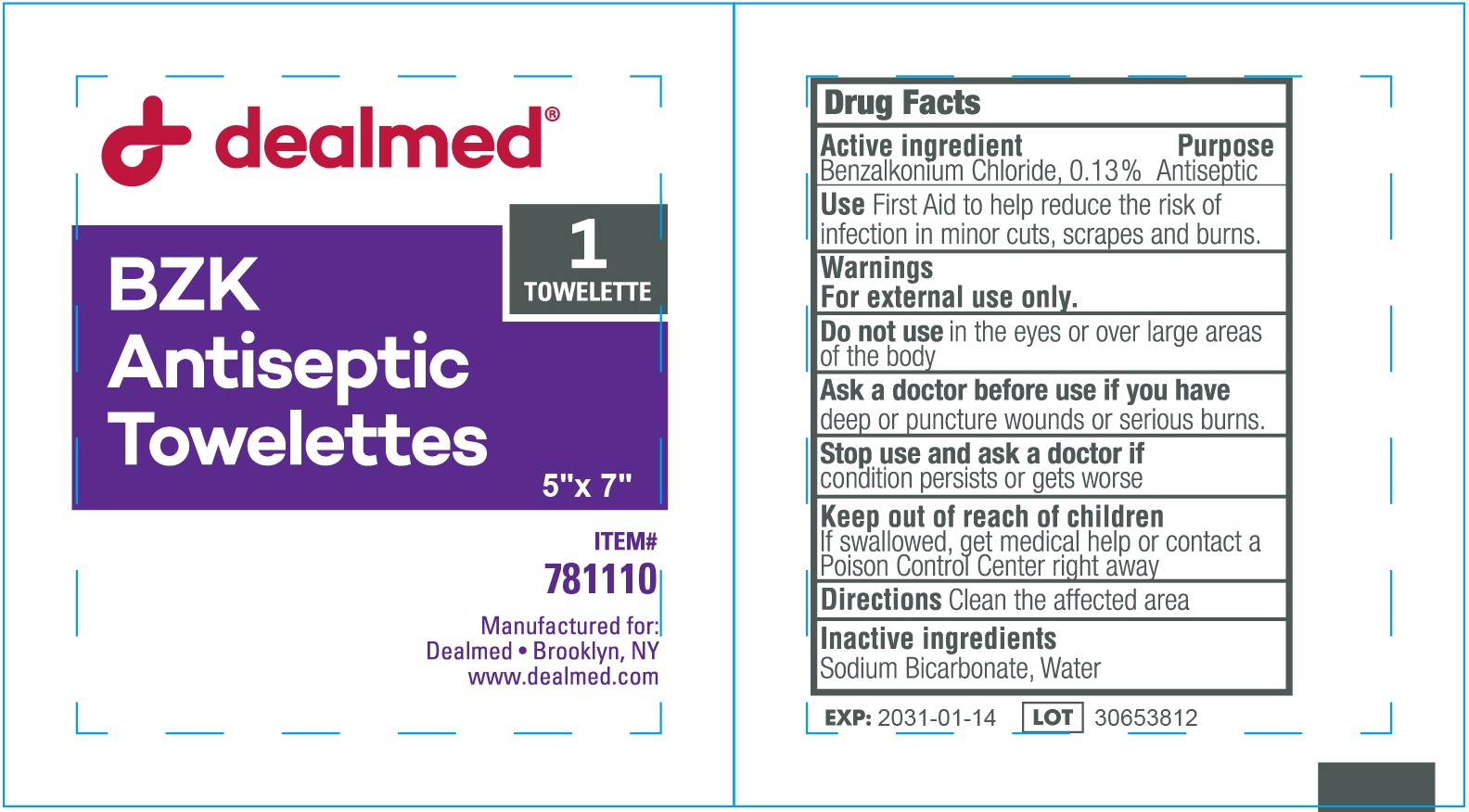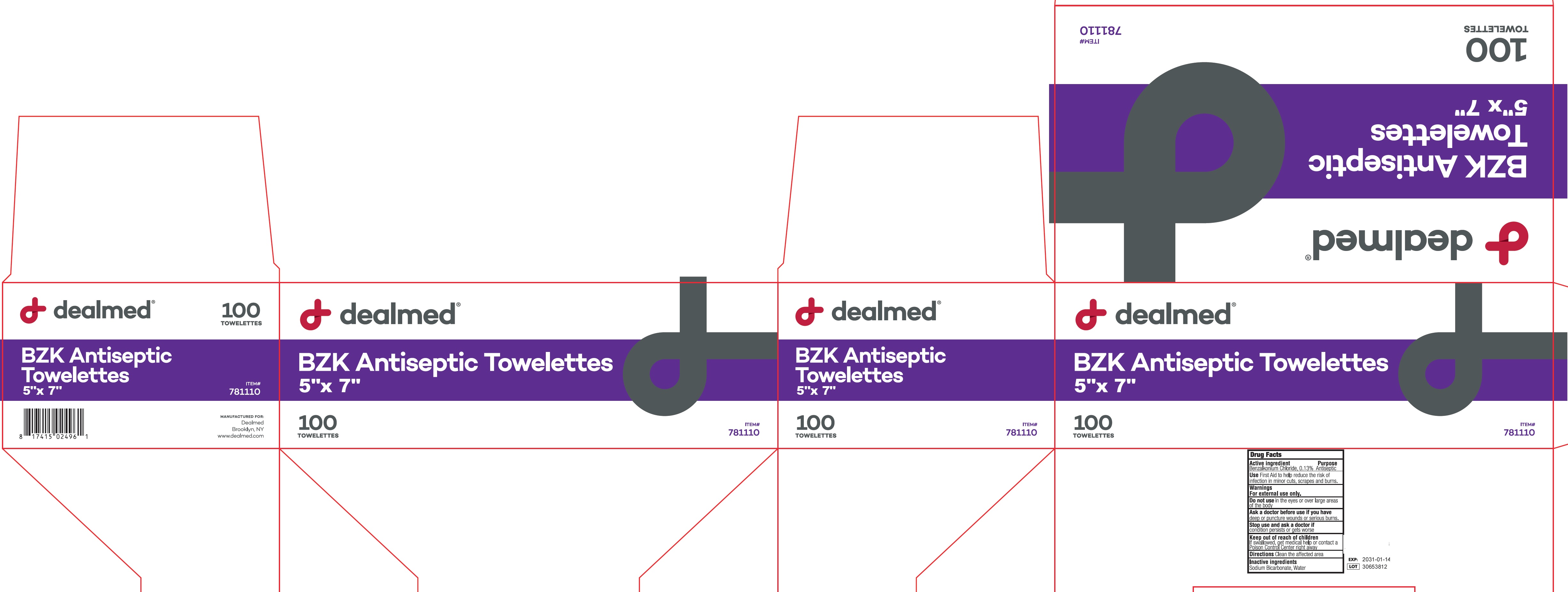 DRUG LABEL: Dealmed BZK Antiseptic Towelettes
NDC: 70082-012 | Form: CLOTH
Manufacturer: Dealmed Medical Supplies, LLC.
Category: otc | Type: HUMAN OTC DRUG LABEL
Date: 20260216

ACTIVE INGREDIENTS: BENZALKONIUM CHLORIDE 1.3 mg/1 mL
INACTIVE INGREDIENTS: SODIUM BICARBONATE; WATER

Dealmed BZK Antiseptic Towelettes

Active ingredient

Benzalkonium Chloride, 0.13%

Purpose

Antiseptic

Use

First Aid to help reduce the risk of infection in minor cuts, scrapes and burns.

Warnings

For external use only.

Do not use

in the eyes or over large areas of the body

Ask a doctor before use if you have

deep or puncture wounds or serious burns.

Stop use and ask a doctor if

condition persists or gets worse

Keep out of reach of children.

If swallowed, get medical help or contact a Poison Control Centre right away

Directions

Clean the affected area

Inactive ingredients

Sodium Bicarbonate, Water